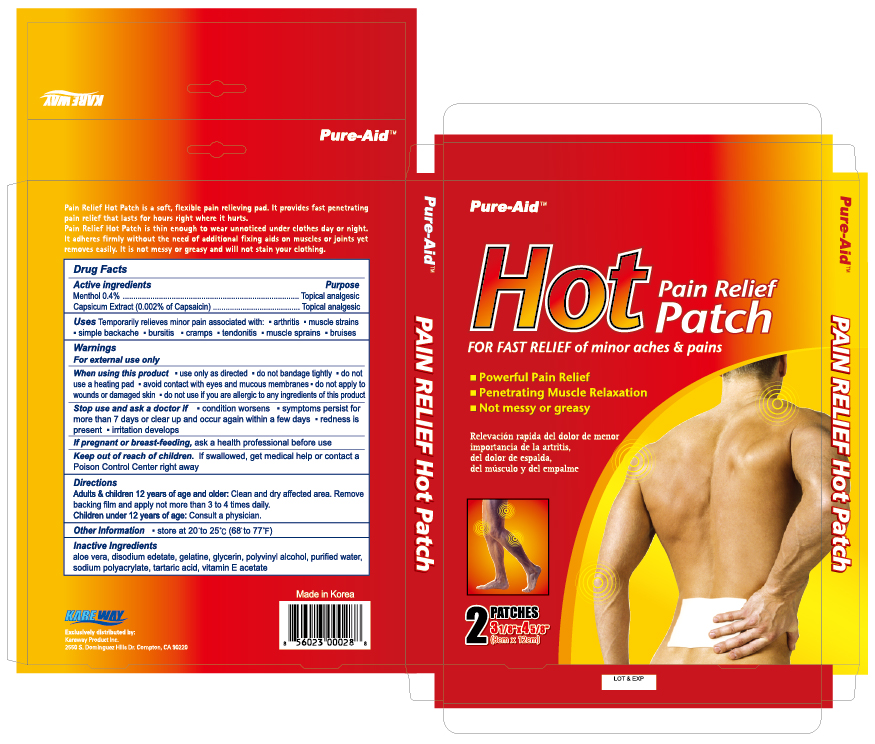 DRUG LABEL: Medicated Pain Relief Hot
NDC: 67510-0226 | Form: PATCH
Manufacturer: Kareway Product, Inc.
Category: otc | Type: HUMAN OTC DRUG LABEL
Date: 20190701

ACTIVE INGREDIENTS: MENTHOL 46.92 mg/1 1; CAPSAICIN 0.25 mg/1 1
INACTIVE INGREDIENTS: WATER; GLYCERIN; EDETATE DISODIUM; TARTARIC ACID; GELATIN; POLYVINYL ALCOHOL; ALPHA-TOCOPHEROL ACETATE; ALOE VERA LEAF

Drug Facts

Active ingredients

L-Menthol 0.4%

Capsicum Extract (0.002% of Capsaicin)

Purposes

Topical analgesic

Topical analgesic

Uses

Temporarily relieves minor pain associated with:

- arthritis
- muscle strains
- simple backache
- bursitis
- cramps
- tendonitis
- muscle sprains
- bruises

Warnings

For external use only

When using this product

- use only as directed
- do not bandage tightly
- do not use a heating pad
- avoid contact with eyes and mucous membrane
- do not apply to wounds or damaged skin
- do not use if you are allergic to any ingredients of this product

Stop use and ask a doctor if

- condition worsens
- symptoms persist for more than 7 days or clear up and occur again within a few days
- redness is present
- irritation develops

If pregnant or breast-feeding,

ask a health professional before use

Keep out of reach of children.

If swallowed, get medical help or contact a Poison Control Center right away

Directions

Adults and children 12 years of age and older: Clean and dry affected area. Remove backing film and apply not more than 3 to 4 times daily.

Children under 12 years of age: Consult a physician.

Other information

store at 20° to 25°C (68° to 77°F)

Inactive ingredients

Purified water, Glycerin, Disodium edetate, Tartaric acid, Gelatine, Polyvinyl alcohol, Sodium polyacrylate, Vitamin E acetate, Aloe vera